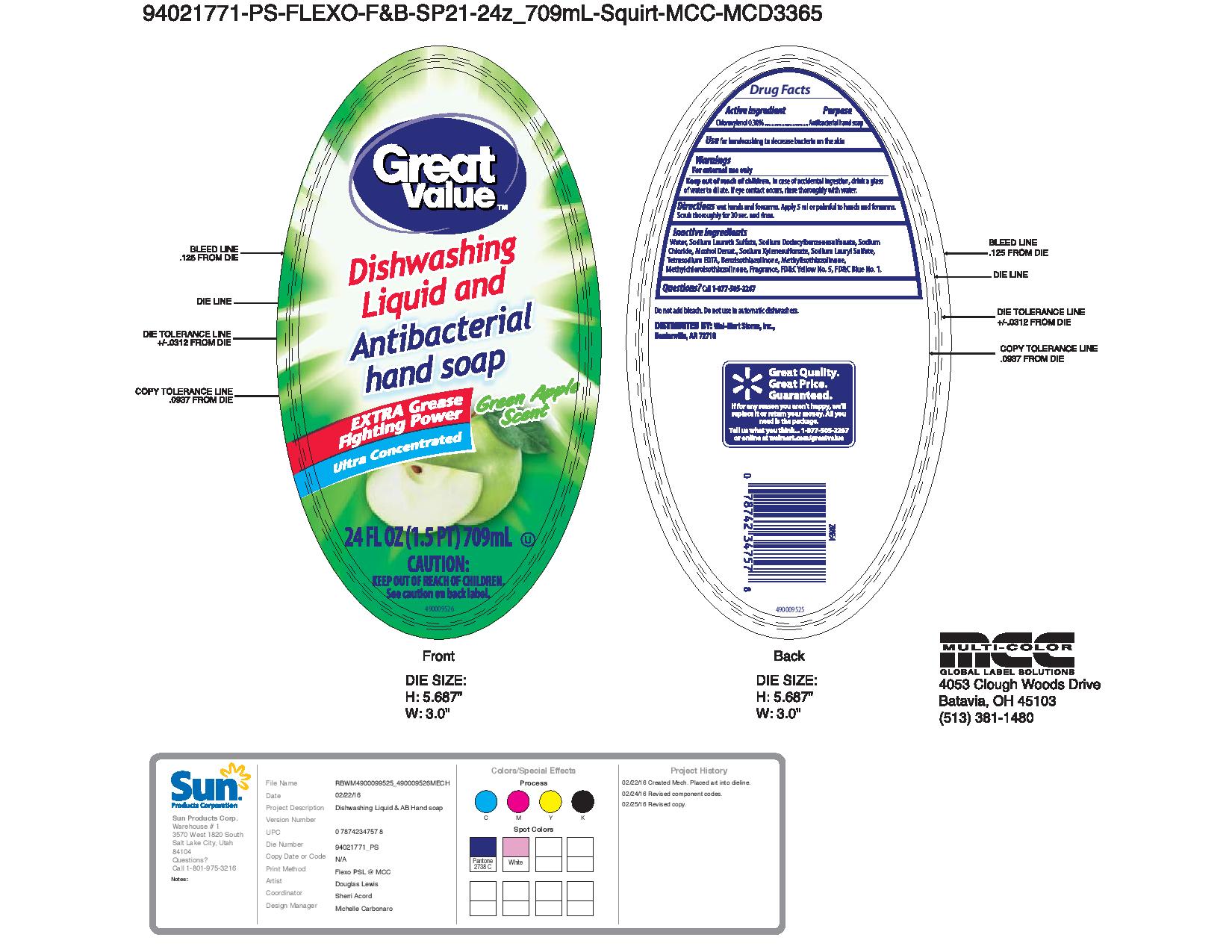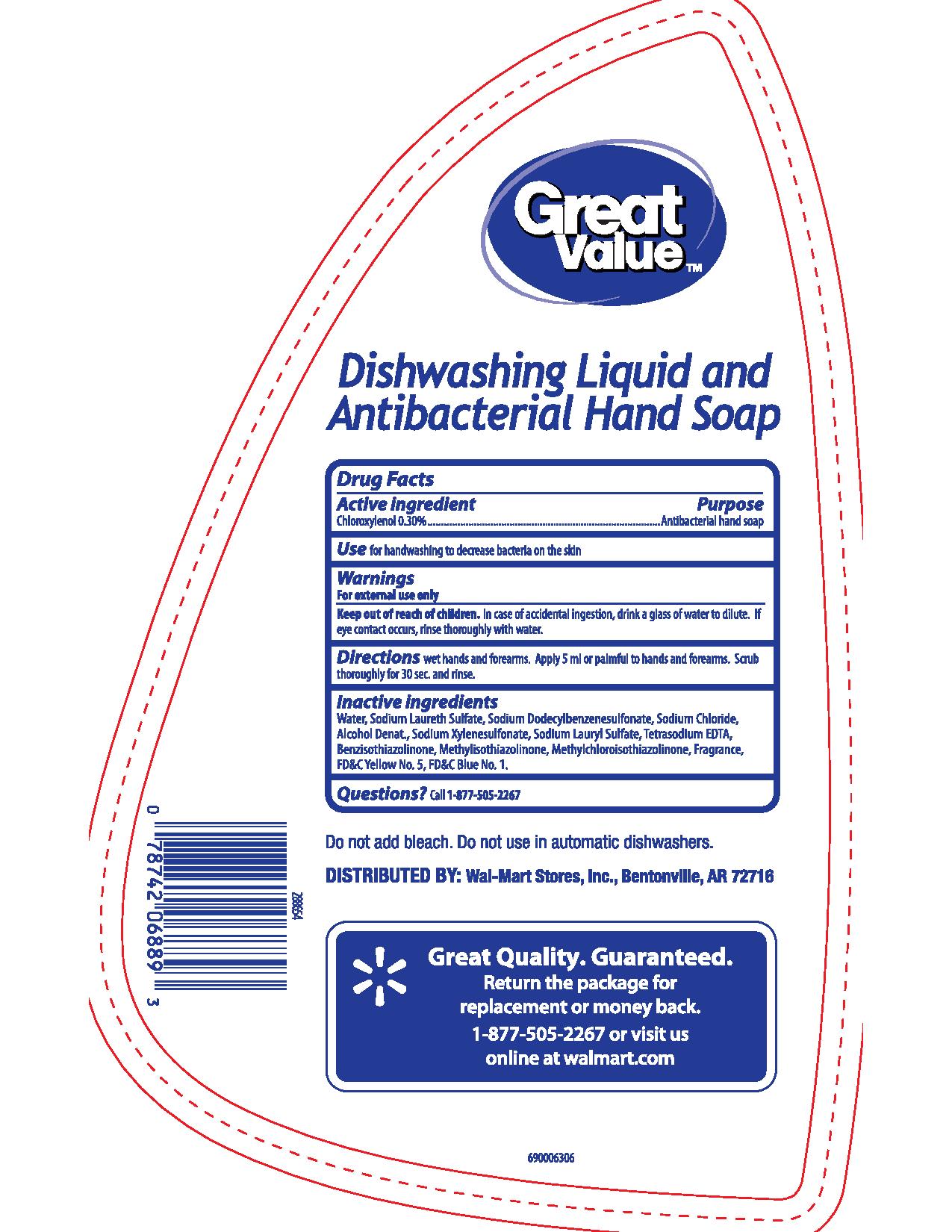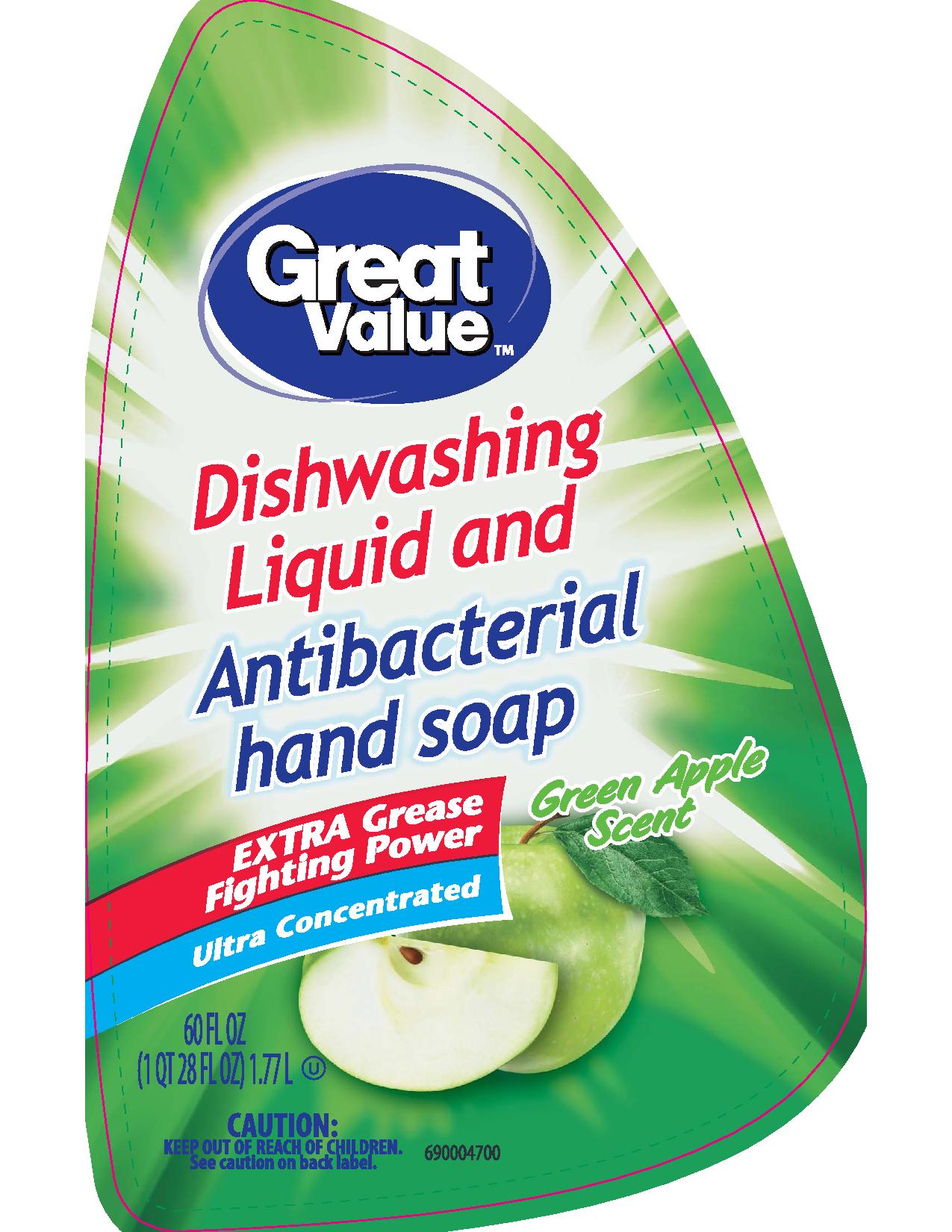 DRUG LABEL: Great Value Green Apple Scent
NDC: 63691-034 | Form: SOAP
Manufacturer: Sun Products Corporation
Category: otc | Type: HUMAN OTC DRUG LABEL
Date: 20170307

ACTIVE INGREDIENTS: CHLOROXYLENOL 0.3 g/100 mL
INACTIVE INGREDIENTS: SODIUM DODECYLBENZENESULFONATE; SODIUM CHLORIDE; FD&C BLUE NO. 1; EDETATE SODIUM; SODIUM XYLENESULFONATE; SODIUM LAURETH SULFATE; BENZISOTHIAZOLINONE; WATER; FD&C YELLOW NO. 5; SODIUM LAURYL SULFATE; METHYLISOTHIAZOLINONE; ALCOHOL; METHYLCHLOROISOTHIAZOLINONE

Active ingredient

Chloroxylenol 0.30%

INDICATIONS AND USAGE

Use for handwashing to decrease bacteria on the skin

WARNINGS

For external use only

Keep out of reach of children. In case of accidental ingestion, drink a glass of water to dilute. If eye contact occurs, rinse thoroughly with water.

DOSAGE AND ADMINISTRATION

Directions wet hands and forearms. Apply 5 ml or palmful to hands and forearms. Scrub thoroughly for 30 sec. and rinse.

PURPOSE

Antibacterial hand soap

INACTIVE INGREDIENT

Inactive ingredients Water, Sodium Laureth Sulfate, Sodium Dodecylbenzenesulfonate, Sodium Chloride, Alcohol Denat., Sodium Xylenesulfonate, Sodium Lauryl Sulfate, Tetrasodium EDTA, Benzisothiazolinone, Methylisothiazolinone, Methylchloroisothiazolinone, Fragrance, FD&C Yellow No. 5, FD&C Blue No. 1

Questions? 1-877-505-2267